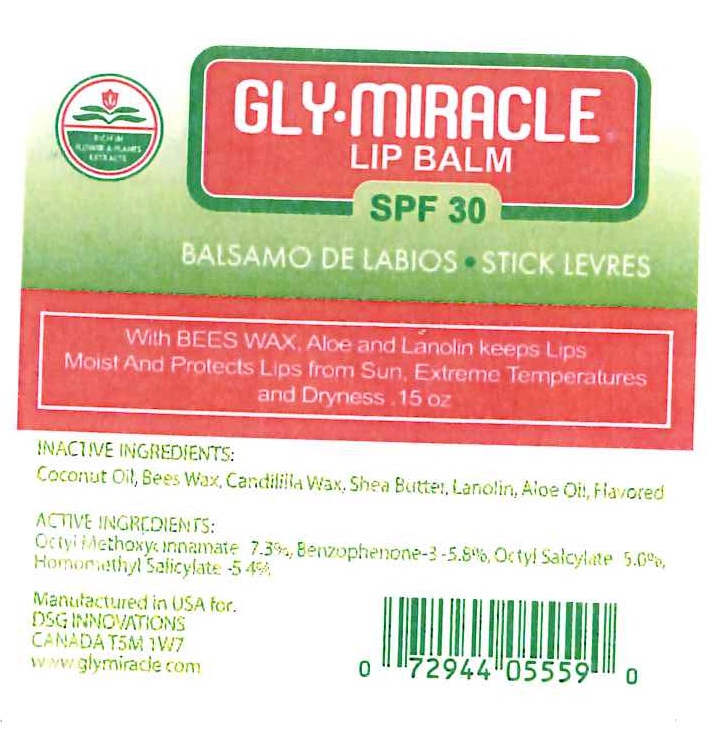 DRUG LABEL: GLY-MIRACLE LIP BALM
NDC: 73537-701 | Form: LIPSTICK
Manufacturer: DSG INNOVATIONS INC
Category: otc | Type: HUMAN OTC DRUG LABEL
Date: 20191230

ACTIVE INGREDIENTS: OCTINOXATE 7.3 g/100 g; OXYBENZONE 5.8 g/100 g; OCTISALATE 5 g/100 g
INACTIVE INGREDIENTS: METHYL SALICYLATE 5.4 g/100 g; COCONUT OIL; YELLOW WAX; CANDELILLA WAX; LANOLIN; ALOE VERA WHOLE; SHEA BUTTER

ACTIVE INGREDIENTS

OCTYL METHOXYCINNAMATE 7.3%, BENZOPHENONE-3 5.8%, OCTYL SALICYLATE 5.0%, HOMOMETHYL SALICYLATE 5.4%

PURPOSE

SUNSCREEN